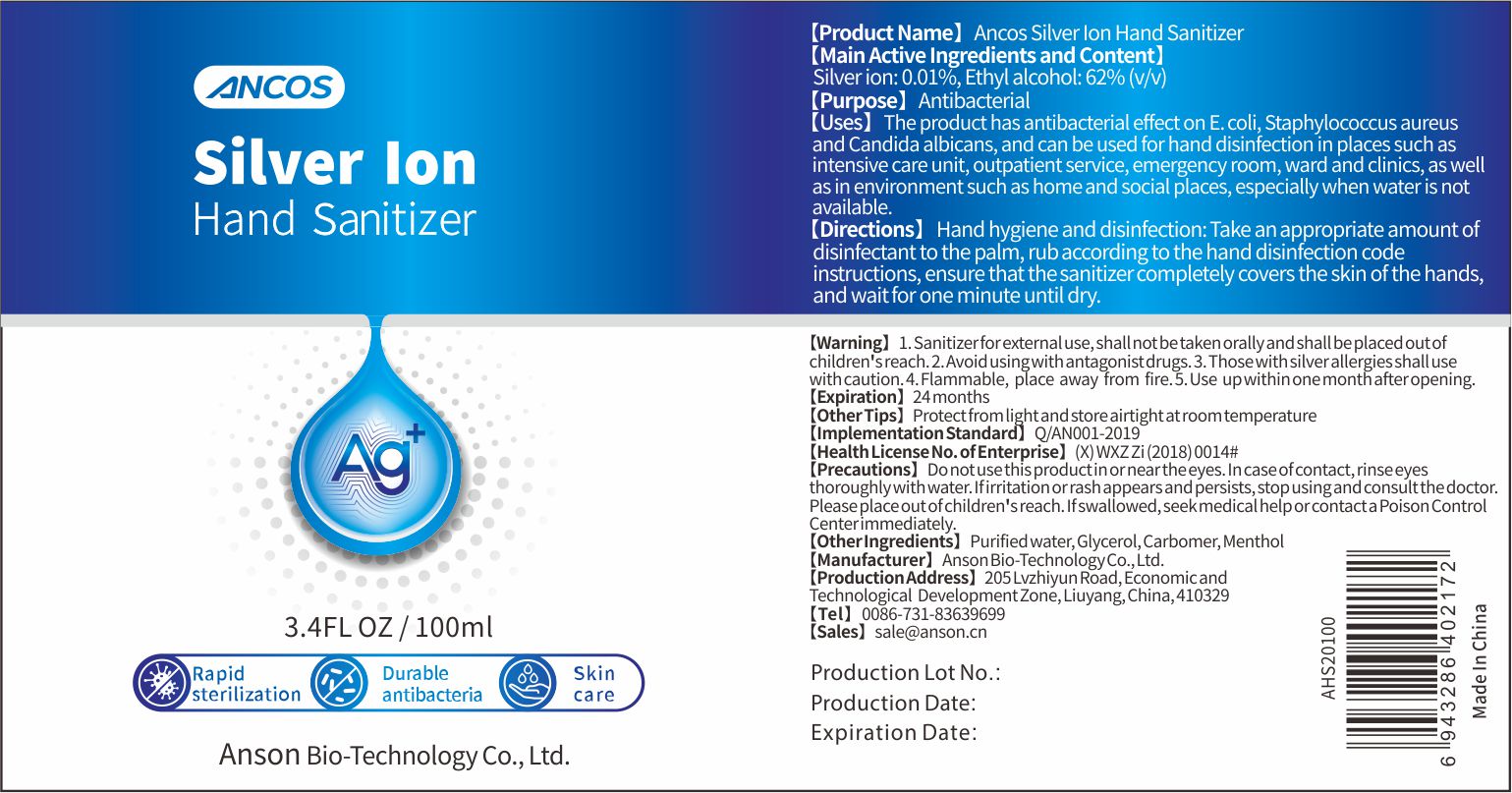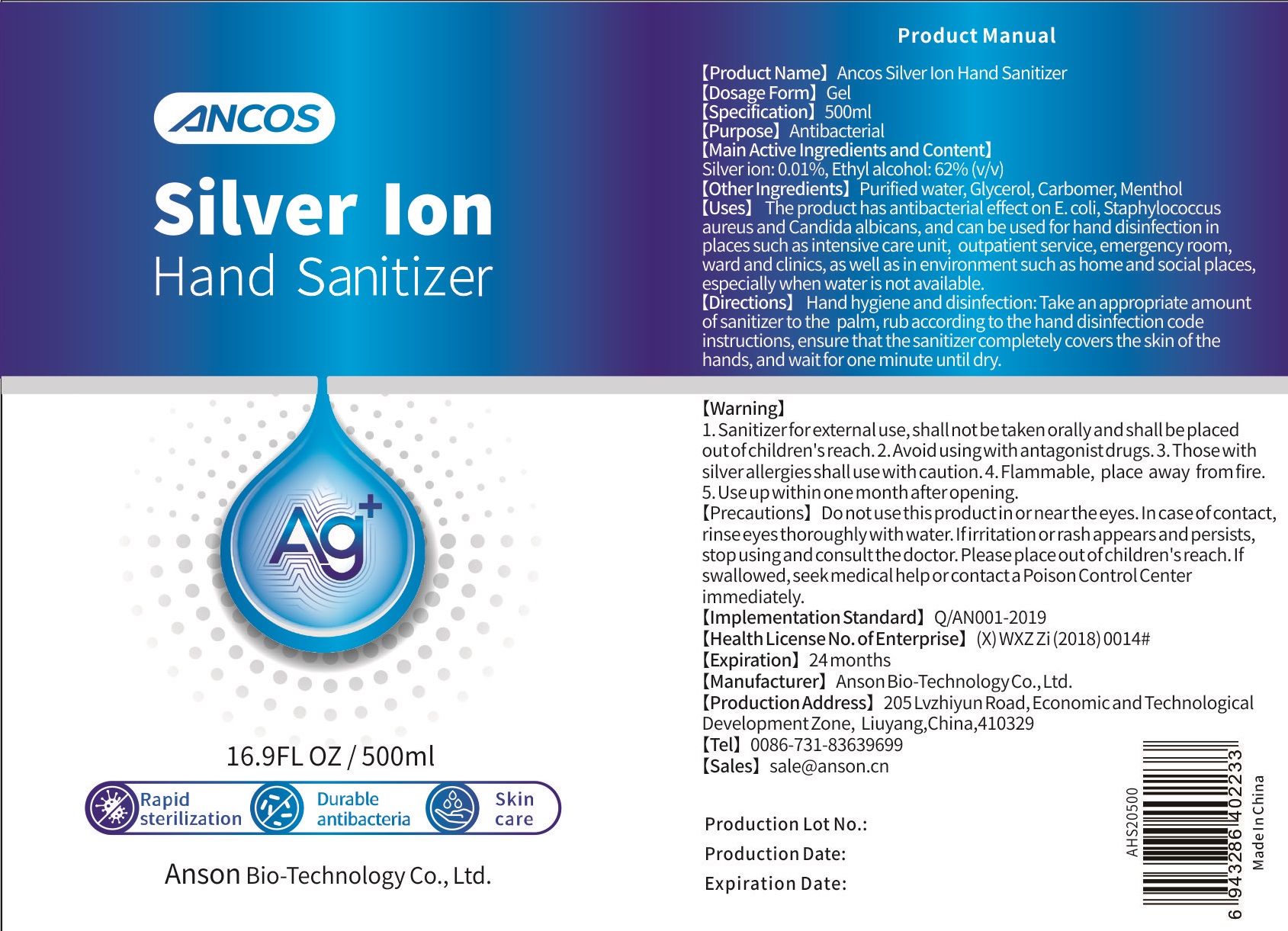 DRUG LABEL: Ancos Silver Ion Hand Sanitizer
NDC: 75139-006 | Form: GEL
Manufacturer: Anson Bio-Technology Co., Ltd.
Category: otc | Type: HUMAN OTC DRUG LABEL
Date: 20200824

ACTIVE INGREDIENTS: SILVER CATION 0.01 g/100 mL; ALCOHOL 62 mL/100 mL
INACTIVE INGREDIENTS: GLYCERIN; MENTHOL; WATER

75139-006
Ancos Silver Ion Hand Sanitizer

Main Active Ingredients and Content

Silver ion: 0.01%, Ethyl alcohol: 62%(v/v)

Purpose

Antibacterial

Uses

The product has antibacterial effect on E coli, Staphylococcus aureus and Candida albicans, and can be used for hand disinfection in places such as intensive care unit, outpatient service, emergency room, ward and clinics, as well as in environment such as home and social places, especially when water is not available

Directions

Hand hygiene and disinfection: Take an appropriate amount of disinfectant to the palm, rub according to the hand disinfection code instructions, ensure that the sanitizer completely covers the skin of the hand sand wait for one minute until dry

Warning

- Sanitizer for external use, shall not betaken orally and shall be placed out of children's reach.
- Avoid using with antagonist drugs
- Those with allergies shall use

Other Tips

Protect from light and store airtight at room temperature

Precautions

Do not use this product in or near the eyes In case of contact, rinse eyes If irritation or rash appears and persists, stop using and consult the doctor.Please place out of children's reach. If swallowed, seek medical help or contact a Poison Control Center immediately

other ingredients

Purified water, Glycerol, Carbomer, Menthol